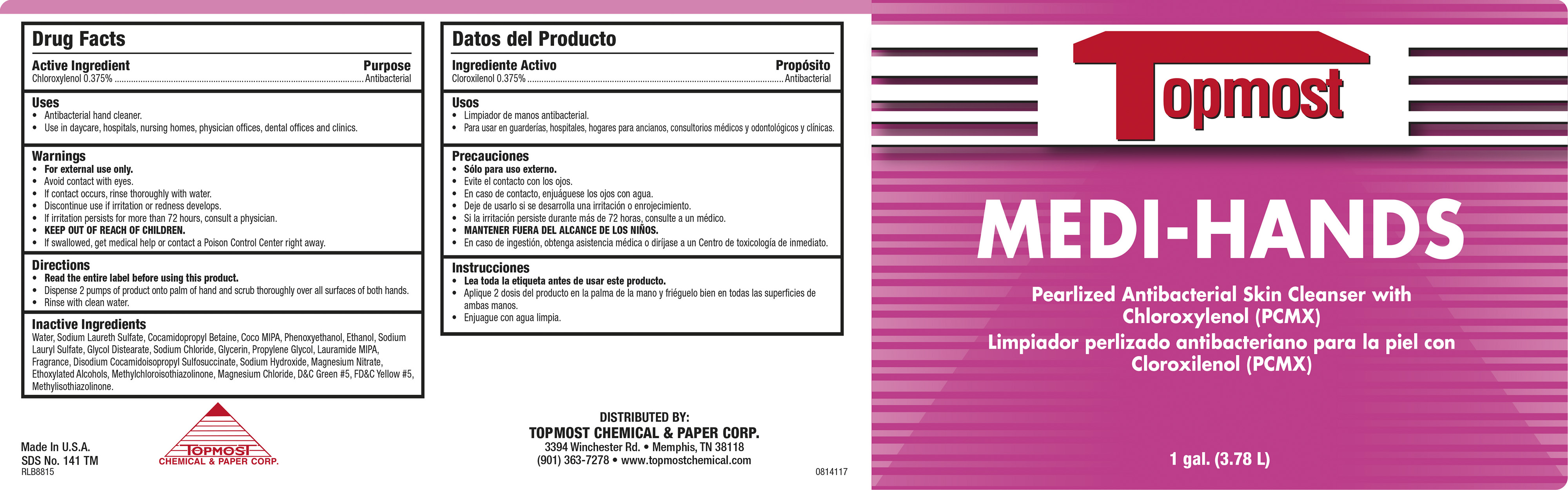 DRUG LABEL: Medi-Hands
NDC: 68978-708 | Form: SOAP
Manufacturer: Topmost Chemical & Paper Corporation
Category: otc | Type: HUMAN OTC DRUG LABEL
Date: 20241226

ACTIVE INGREDIENTS: CHLOROXYLENOL 3.75 mg/1 mL
INACTIVE INGREDIENTS: WATER; SODIUM LAURYL SULFATE; COCO DIETHANOLAMIDE; COCAMIDOPROPYL BETAINE; PHENOXYETHANOL; PROPYLENE GLYCOL; BENZYL BENZOATE; LAURIC DIETHANOLAMIDE; LAURIC ISOPROPANOLAMIDE; D&C GREEN NO. 5; FD&C YELLOW NO. 5; METHYLISOTHIAZOLINONE; METHYL ALCOHOL; ETHYLENE OXIDE; ETHYL METHYLPHENYLGLYCIDATE; CHLOROACETIC ACID; DIOXANE; CALCIUM SILICATE; SODIUM FERROCYANIDE; DIMETHYL BENZYL CARBINYL ACETATE; GLYCOL DISTEARATE; TRIBASIC CALCIUM PHOSPHATE; MAGNESIUM NITRATE; ETHYL BUTYRATE; MYRCENE; SODIUM HYDROXIDE; METHYL ANTHRANILATE; SODIUM ALUMINIUM SILICATE; ETHYL ACETOACETATE; METHYLCHLOROISOTHIAZOLINONE; SODIUM CARBONATE; .GAMMA.-DECALACTONE; LINALOOL, (+/-)-; DIMETHYL BENZYL CARBINYL BUTYRATE

Medi-Hands

Medi-Hands

Active Ingredient

Chloroxylenol 0.375%

Medi-Hands

Uses

- Antibacterial hand cleaner.
- Use in daycare, hospitals, nursing homes, physicians offices, dental offices and clinics

Medi-Hands

Warnings

- For external use only.
- Avoid contact with eyes.
- Children under the age of 6 should be supervised by an adult when using this product.
- Discontinue use is irritation or redness develops.
- If irritation persists for more than 72 hours, consult a physician.
- KEEP OUT OF REACH OF CHILDREN.

Medi-Hands

Directions

- Read the entire label before using this product.
- Dispense 1-2 pumps of product onto wet palm.
- Lather and rinse hands with clean water

Medi-Hands

Inactive Ingredients

Water, Sodium Lauryl lSulfate, Cocamide DEA, Cocamidopropyl betadine, Phenoxyethanol, Sodium Laureth Sulfate, Propylene Glycol, Fragrance, DMDM Hydantoin, Glycol Stearate, Laurimide DEA, Glycerine, Tocopheryl Acetate, D&C Green #5, FD&C Yellow #5.

Medi-Hands

Purpose

Antibacterial

Medi-Hands

KEEP OUT OF REACH OF CHILDREN

Medi-Hands Pearlized Antibacterial Skin Cleanser with PCMX Distributed by: TOPMOST CHEMICAL & PAPER CORP. 3394 Winchester Rd. Memphis, TN 38118 (901) 363-7278

14104-00_Topmost_MediHands